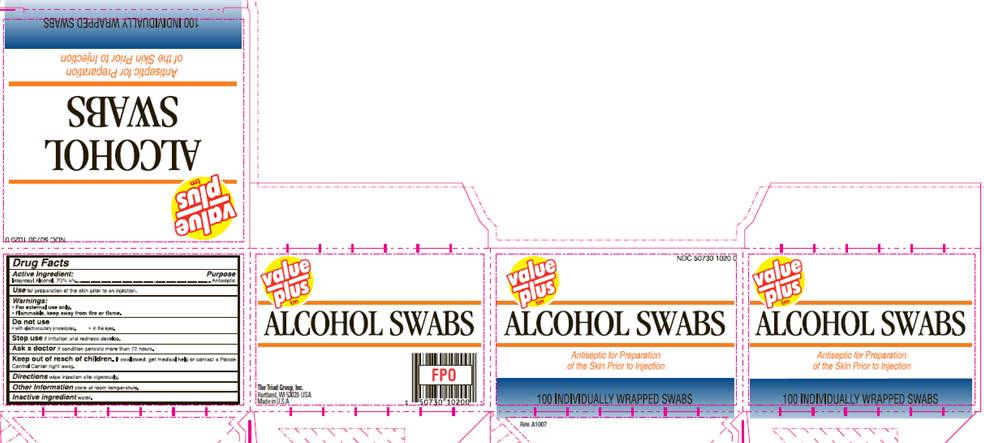 DRUG LABEL: Isopropyl Alcohol Swabs
NDC: 50730-1020 | Form: SWAB
Manufacturer: H and P Industries, Inc. dba Triad Group
Category: otc | Type: HUMAN OTC DRUG LABEL
Date: 20091211

ACTIVE INGREDIENTS: Isopropyl alcohol .7 mL/1 1
INACTIVE INGREDIENTS: water

DRUG FACTS

ACTIVE INGREDIENT

Isopropyl Alcohol 70% v/v

PURPOSE

Antiseptic

USE

For preparation of the skin prior to an injection

WARNINGS

For external use only.
Flammable, keep away from fire or flame.

Do not use

- with electrocautery procedures
- in the eyes

Stop use

if irritation and redness develop.

Ask a doctor

if condition persists for more than 72 hours.

Keep out of reach of children

If swallowed, get medical help or contact a Poison Control Center right away.

DIRECTIONS

Wipe injection site vigorously

OTHER INFORMATION

Store at room temperature

INACTIVE INGREDIENT

water

PACKAGE INFORMATION

NDC 50730-1020-0

value plus

ALCOHOL SWABS

Antiseptic for Preparation
of the Skin Prior to Injection

100 INDIVIDUALLY WRAPPED SWABS
The Triad Group, Inc.
Hartland, WI 53029 USA
Made in USA